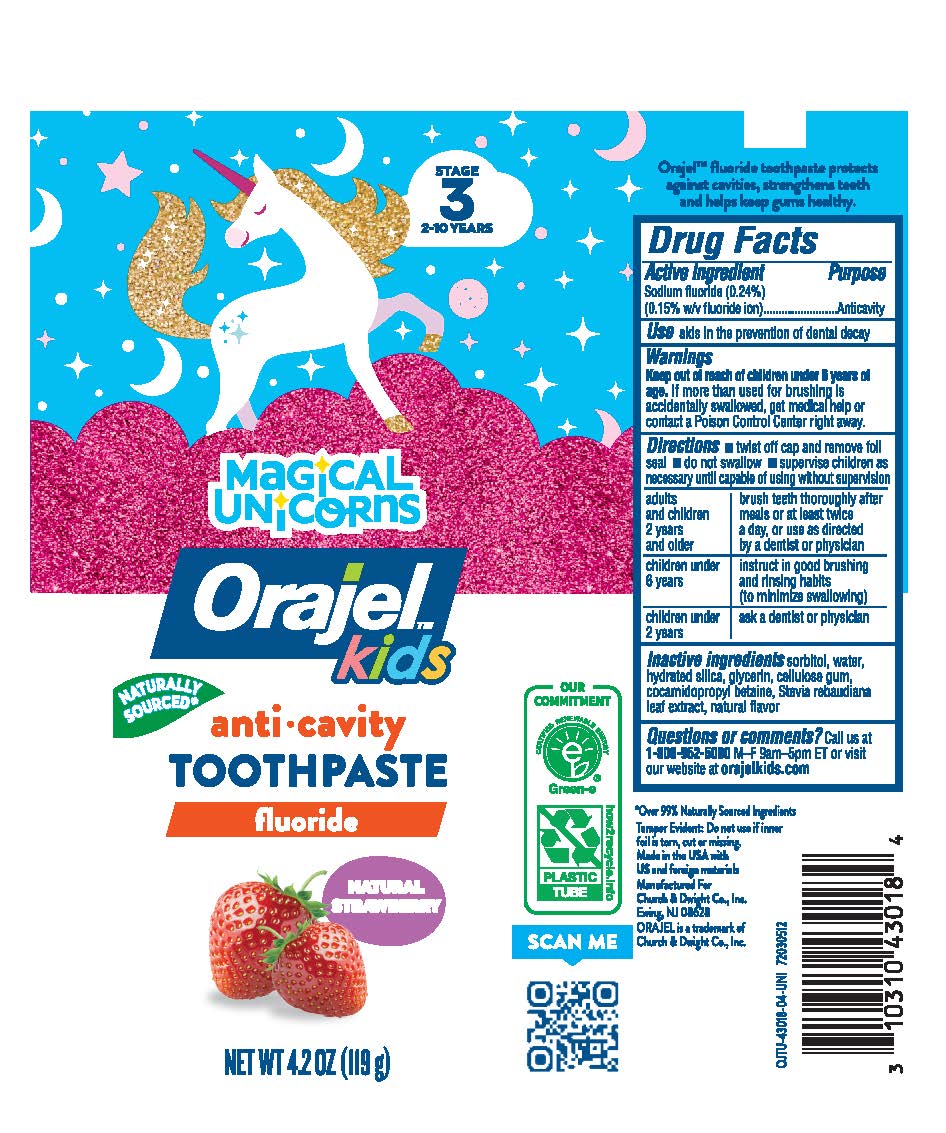 DRUG LABEL: Orajel KidsToothpaste
NDC: 10237-785 | Form: PASTE, DENTIFRICE
Manufacturer: Church & Dwight Co., Inc.
Category: otc | Type: HUMAN OTC DRUG LABEL
Date: 20251212

ACTIVE INGREDIENTS: SODIUM FLUORIDE 1.5 mg/1 g
INACTIVE INGREDIENTS: SORBITOL; WATER; HYDRATED SILICA; GLYCERIN; CARBOXYMETHYLCELLULOSE SODIUM, UNSPECIFIED; COCAMIDOPROPYL BETAINE; STEVIA REBAUDIANA LEAF

Orajel Mermaid and Unicorn Fluoride Toothpaste

Active ingredient

Sodium fluoride 0.24%

(0.15% w/v fluoride ion)

Purpose

Anticavity

Use

aids in the prevention of dental decay

Warnings

Keep out of reach of children under 6 years of age. If more than used for brushing is accidentally swallowed, get medical help or contact a Poison Control Center right away.

Directions

- twist off cap and remove foil seal
- do not swallow
- supervise children as necessary until capable of using without supervision

adults and children 2 years and older | brush teeth thoroughly after meals or at least twice a day, or use as directed by a dentist or physician
children under 6 years | instruct in good brushing and rinsing habits (to minimize swallowing)
children under 2 years | ask a dentist of physician

Inactive ingredients

sorbitol, water, hydrated silica, glycerin, cellulose gum, cocamidopropyl betaine, Stevia rebaudiana leaf extract, natural flavor

Questions or comments?

Call us at 1-800-952-5080 M-F 9am-5pm ET or visit our website at orajelkids.com

OTHER SAFETY INFORMATION

Tamper Evident: Do not use if inner foil is torn, cut or missing.

Principal Display Panel

NATURAL STRAWBERRY

magical unicorns OR mermaid

Orajel kids

Anti•cavity

TOOTHPASTE

Fluoride

NET WT 4.2 OZ (119 g)